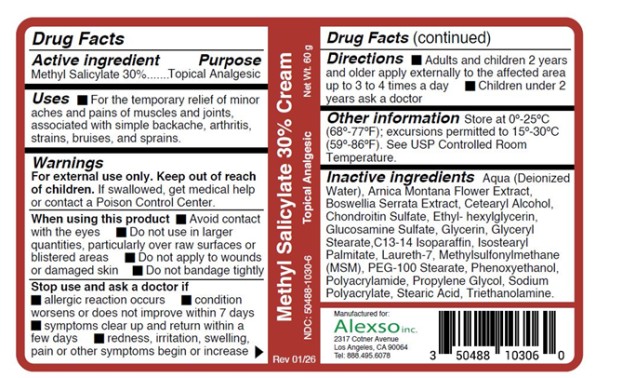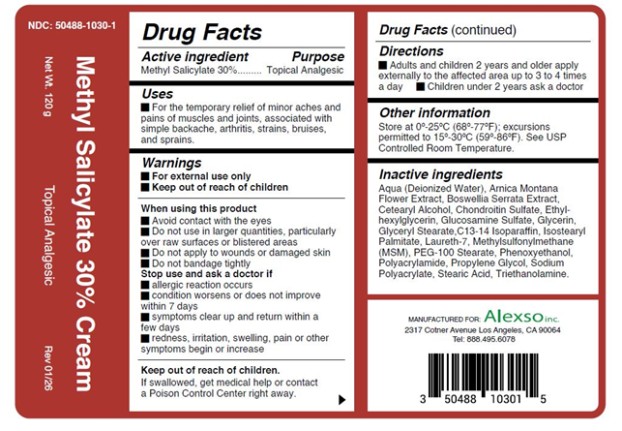 DRUG LABEL: Methyl Salicylate 30 Percent Cream
NDC: 50488-1030 | Form: CREAM
Manufacturer: Alexso, Inc
Category: otc | Type: HUMAN OTC DRUG LABEL
Date: 20260213

ACTIVE INGREDIENTS: METHYL SALICYLATE 30 g/100 g
INACTIVE INGREDIENTS: WATER; ARNICA MONTANA FLOWER; BOSWELLIA SERRATA GUM; CETEARYL ALCOHOL; ETHYLHEXYLGLYCERIN; GLUCOSAMINE SULFATE; GLYCERIN; GLYCERYL STEARATE; C13-14 ISOPARAFFIN; ISOSTEARYL PALMITATE; LAURETH-7; DIMETHYL SULFONE; PEG-100 STEARATE; PHENOXYETHANOL; PROPYLENE GLYCOL; STEARIC ACID; TRIETHANOLAMINE; CHONDROITIN SULFATE (BOVINE); POLYACRYLAMIDE (10000 MW); SODIUM POLYACRYLATE (8000 MW)

Methyl Salicylate 30 Percent Cream

Drug Facts

Active ingredient

Methyl Salicylate 30%

Purpose

Topical analgesic

Uses

For the temporary relief of minor aches and pains of muscles and joints, associated with simple backache, arthritis, strains, bruises, and sprains.

Warnings

For external use only.

When using this product

- Avoid contact with the eyes
- Do not use in large quantities, particularly over raw surfaces or blistered areas
- Do not apply to wounds or damaged skin
- Do not bandage tightly

Stop use and ask a doctor if

- allergic reaction occurs
- condition worsens or does not improve within 7 days
- symptoms clear up and return within a few days
- redness, irritation, swelling, pain or other symptoms begin or increase

Keep out of reach of children.

If swallowed, get medical help or contact a Poison Control Center right away.

Directions

adults and children 2 years and older | apply externally to the affected area up to 3 to 4 times a day
children under 2 years | ask a doctor

Other information

- Store at 20-25°C (68-77°F); excursions permitted to 15-30°C (59-86°F). See USP Controlled Room Temperature.

Inactive ingredients

Aqua (Deionized Water), Arnica Montana Flower Extract, Boswellia Serrata Extract, Cetearyl Alcohol, Chondroitin Sulfate, Ethylhexylglycerin, Glucosamine Sulfate, Glycerin, Glyceryl Stearate, C13-14 Isoparaffin, Isostearyl Palmitate, Laureth-7, Methylsulfonylmethane (MSM), PEG-100 Stearate, Phenoxyethanol, Polyacrylamide, Propylene Glycol, Sodium Polyacrylate, Stearic Acid, Triethanolamine

PRINCIPAL DISPLAY PANEL

Methyl Salicylate 30% Cream

NDC: 50488-1030-6

60 grams

PRINCIPAL DISPLAY PANEL

Methyl Salicylate 30% Cream

NDC: 50488-1030-1

120 grams

Manufactured for:
Alexso, Inc
Los Angeles, CA 90064